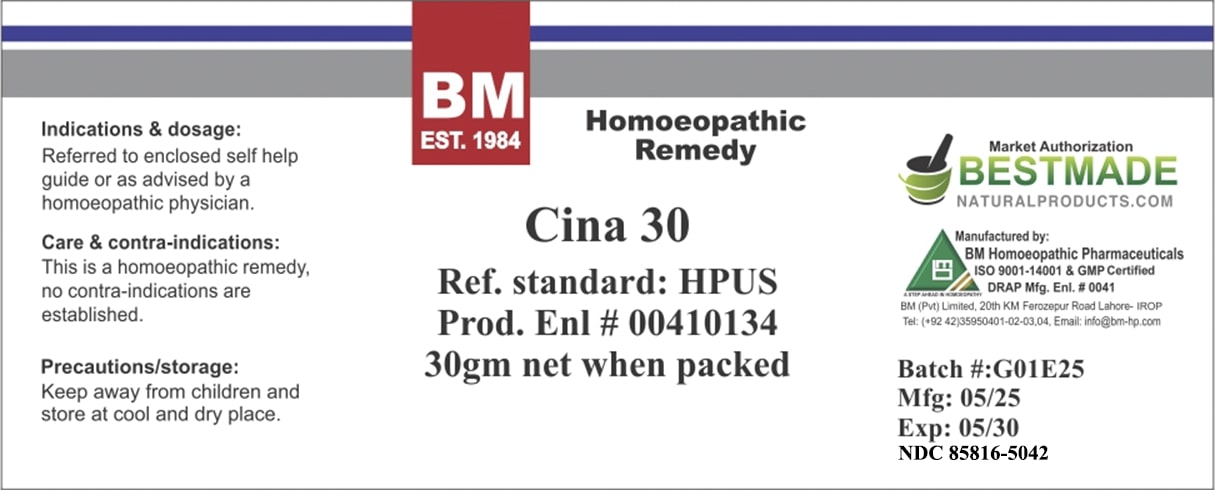 DRUG LABEL: BM Cina
NDC: 85816-5042 | Form: GLOBULE
Manufacturer: BM Private Limited
Category: homeopathic | Type: HUMAN OTC DRUG LABEL
Date: 20250701

ACTIVE INGREDIENTS: ARTEMISIA CINA FLOWER 30 [hp_C]/1000 mg
INACTIVE INGREDIENTS: SUCROSE 1000 mg/1000 mg

BM Cina 30C

ACTIVE INGREDIENT

Cina

INACTIVE INGREDIENT

sucrose

Indications & dosage:
Referred to enclosed self help guide or as advised by a homoeopathic physician.

Indications & dosage:
Referred to enclosed self help guide or as advised by a homoeopathic physician.

PURPOSE

Indications & dosage:
Referred to enclosed self help guide or as advised by a homoeopathic physician.

WARNINGS

Precautions/storage:
Keep away from children and store at cool and dry place.

KEEP OUT OF REACH OF CHILDREN

Precautions/storage:
Keep away from children and store at cool and dry place.

CONTRAINDICATIONS

Care & contra-indications:
This is a homoeopathic remedy, no contra-indications are established.

Entire package label